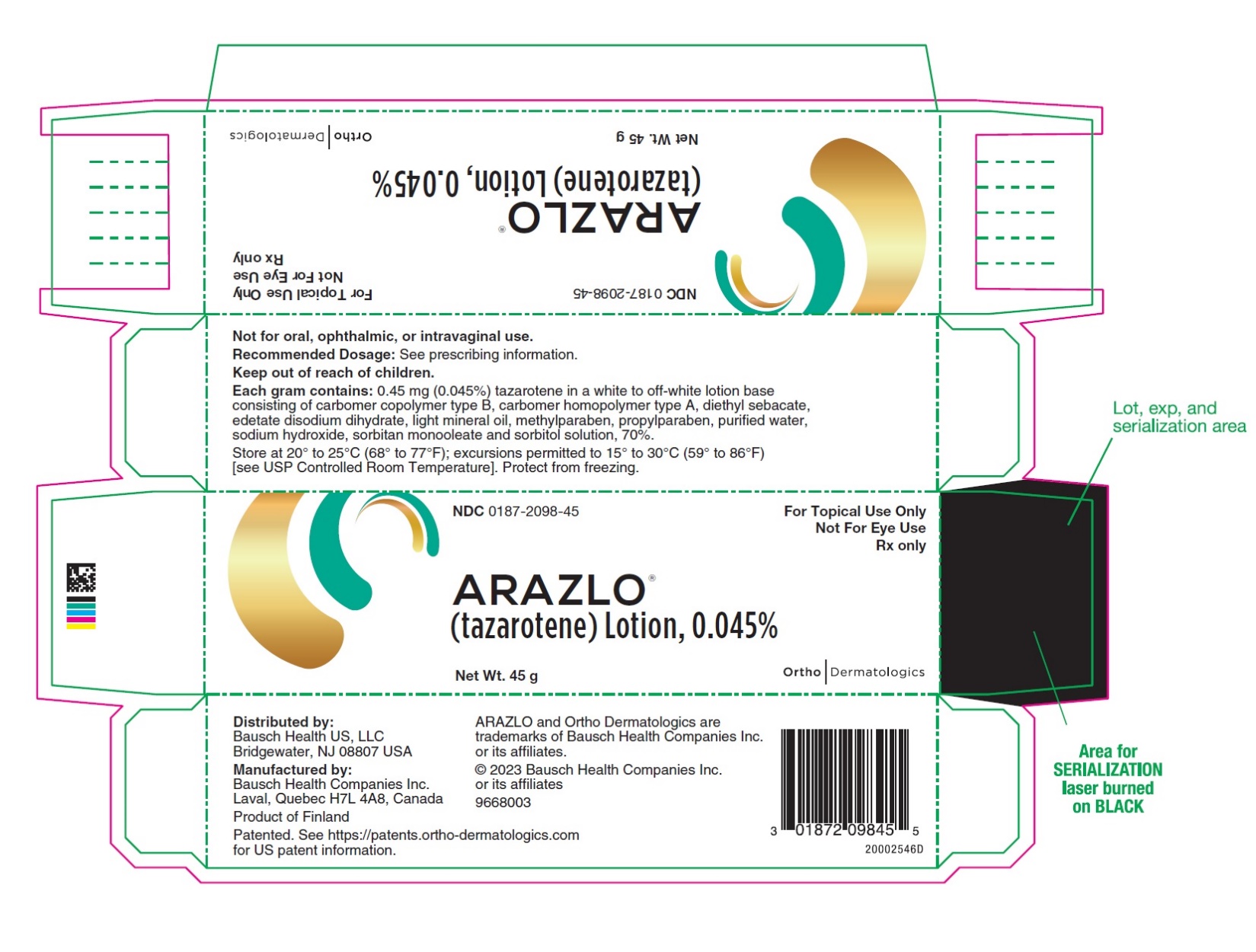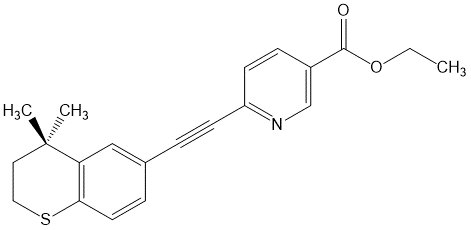 DRUG LABEL: Arazlo
NDC: 0187-2098 | Form: LOTION
Manufacturer: Bausch Health US, LLC
Category: prescription | Type: HUMAN PRESCRIPTION DRUG LABEL
Date: 20230926

ACTIVE INGREDIENTS: TAZAROTENE 0.45 mg/1 g
INACTIVE INGREDIENTS: CARBOMER COPOLYMER TYPE B (ALLYL PENTAERYTHRITOL CROSSLINKED); CARBOMER HOMOPOLYMER TYPE A (ALLYL PENTAERYTHRITOL CROSSLINKED); DIETHYL SEBACATE; EDETATE DISODIUM; LIGHT MINERAL OIL; METHYLPARABEN; PROPYLPARABEN; WATER; SODIUM HYDROXIDE; SORBITAN MONOOLEATE; SORBITOL

HIGHLIGHTS OF PRESCRIBING INFORMATION

These highlights do not include all the information needed to use ARAZLO safely and effectively. See full prescribing information for ARAZLO.
ARAZLO®(tazarotene) lotion, for topical use
Initial U.S. Approval: 1997

1 INDICATIONS AND USAGE

ARAZLO is a retinoid indicated for the topical treatment of acne vulgaris in patients 9 years of age and older. (1)

2 DOSAGE AND ADMINISTRATION

- Apply a thin layer of ARAZLO to the affected areas once daily. Avoid the eyes, mouth, paranasal creases, and mucous membranes. (2)
- Not for oral, ophthalmic, or intravaginal use. (2)

3 DOSAGE FORMS AND STRENGTHS

Lotion, 0.045% (3)

4 CONTRAINDICATIONS

ARAZLO is contraindicated in pregnancy. (4, 8.1)

5 WARNINGS AND PRECAUTIONS

- Embryofetal Toxicity: May cause fetal harm when administered during pregnancy. Patients of childbearing potential should have a negative pregnancy test within 2 weeks prior to initiating treatment and use effective contraception during treatment. (5.1)
- Skin Irritation: Pain, dryness, exfoliation, erythema, and pruritus may occur with use of ARAZLO. Avoid application to eczematous or sunburned skin. (5.2)
- Photosensitivity and Risk for Sunburn: Minimize exposure to sunlight and sunlamps. Use sunscreen and protective clothing when sun exposure cannot be avoided. Administer with caution if the patient is also taking drugs known to be photosensitizers. (5.3)

6 ADVERSE REACTIONS

- The most common adverse reactions (occurring in ≥1% of the ARAZLO group and greater than the vehicle group) were application site reactions; pain, dryness, exfoliation, erythema and pruritus. (6.1)

To report SUSPECTED ADVERSE REACTIONS, contact Bausch Health US, LLC at 1-800-321-4576 or FDA at 1-800-FDA-1088 or www.fda.gov/medwatch.

FULL PRESCRIBING INFORMATION

1 INDICATIONS AND USAGE

ARAZLO®(tazarotene) lotion, 0.045% is indicated for the topical treatment of acne vulgaris in patients 9 years of age and older.

2 DOSAGE AND ADMINISTRATION

Apply a thin layer of ARAZLO to the affected areas once daily. Avoid the eyes, mouth, paranasal creases, and mucous membranes. If ARAZLO gets in or near eyes, rinse thoroughly with water.

ARAZLO is for topical use only. Not for oral, ophthalmic, or intravaginal use.

Wash hands thoroughly after applying ARAZLO.

Avoid concomitant use with oxidizing agents, such as benzoyl peroxide. If the concomitant use of ARAZLO with oxidizing agents is required, apply each at different times of the day (e.g. one in the morning and the other in the evening) [see Drug Interactions (7)] .

Use effective sunscreens and wear protective clothing while using ARAZLO [see Warnings and Precautions (5.3)] .

3 DOSAGE FORMS AND STRENGTHS

Lotion, 0.045%

Each gram of ARAZLO contains 0.45 mg (0.045%) tazarotene in a white to off-white topical lotion.

4 CONTRAINDICATIONS

ARAZLO is contraindicated in pregnancy. ARAZLO may cause fetal harm when administered to a pregnant patient [see Warnings and Precautions (5.1), Use in Specific Populations (8.1, 8.3)] .

5 WARNINGS AND PRECAUTIONS

5.1 Embryofetal Toxicity

Based on data from animal reproduction studies, retinoid pharmacology and the potential for systemic absorption, ARAZLO may cause fetal harm when administered to a pregnant patient and is contraindicated during pregnancy .Safety in pregnant patients has not been established. The potential risk to the fetus outweighs the potential benefit to the mother; therefore, discontinue ARAZLO as soon as pregnancy is recognized.

Tazarotene elicits malformations and developmental effects associated with retinoids after topical and oral administration to pregnant rats and rabbits during organogenesis. However, limited case reports of pregnancy in females enrolled in clinical trials for ARAZLO have not reported a clear association with tazarotene and major birth defects or miscarriage risk [see Contraindications (4), Use in Specific Populations (8.1)] .

Systemic exposure to tazarotenic acid is dependent upon the extent of the body surface area treated. In patients treated topically over sufficient body surface area, exposure could be in the same order of magnitude as in orally treated animals. Tazarotene is a teratogenic substance in animals, and it is not known what level of exposure is required for teratogenicity in humans.

Advise pregnant patients of the potential risk to a fetus. Obtain a pregnancy test within 2 weeks prior to ARAZLO therapy. Initiate ARAZLO therapy during a menstrual period. Advise patients of childbearing potential to use effective contraception during treatment with ARAZLO [see Dosage and Administration (2), Use in Specific Populations (8.3)] .

5.2 Skin Irritation

Patients using ARAZLO may experience application site pain, dryness, exfoliation, erythema, and pruritus. Depending upon severity of these adverse reactions, instruct patients to use a moisturizer, reduce the frequency of the application of ARAZLO, or discontinue use. Therapy can be resumed, or the frequency of application can be increased, as the patient becomes able to tolerate treatment.

Avoid use of concomitant medications and cosmetics that have a strong drying effect. It is recommended to postpone treatment with ARAZLO until the drying effects of these products subside.

Avoid application of ARAZLO to eczematous or sunburned skin.

5.3 Photosensitivity and Risk for Sunburn

Because of heightened burning susceptibility, minimize unprotected exposure to ultraviolet light including sunlight and sunlamps during the use of ARAZLO. Warn patients who normally experience high levels of sun exposure and those with inherent sensitivity to sun to exercise caution. Use sunscreen products and protective clothing over treated areas when sun exposure cannot be avoided. Patients with sunburn should be advised not to use ARAZLO until fully recovered.

ARAZLO should be administered with caution if the patient is taking drugs known to be photosensitizers (e.g., thiazides, tetracyclines, fluoroquinolones, phenothiazines, sulfonamides) because of the increased possibility of augmented photosensitivity.

Weather extremes, such as wind or cold, may be more irritating to patients using ARAZLO.

6 ADVERSE REACTIONS

The following serious adverse reactions are discussed in more detail in other sections of the labeling:

- Embryofetal toxicity [see Warnings and Precautions (5.1)]
- Photosensitivity and Risk of Sunburn [see Warnings and Precautions (5.3)]

6.1 Clinical Trials Experience

Because clinical trials are conducted under widely varying conditions, adverse reaction rates observed in the clinical trials of a drug cannot be directly compared to rates in the clinical trials of another drug and may not reflect the rates observed in clinical practice.

In 2 multicenter, randomized, double-blind, vehicle-controlled clinical trials, subjects age 9 years and older applied ARAZLO or vehicle once daily for 12 weeks. The majority of subjects were White (74%) and female (66%). Approximately 22% were Hispanic/Latino and 42% were younger than 18 years of age, fourteen of 779 subjects (1.8%) treated with ARAZLO were between 9 years to less than 12 years of age. Adverse reactions reported by ≥1% of subjects treated with ARAZLO and more frequently than subjects treated with vehicle are summarized in Table 1. Most adverse reactions were mild to moderate in severity. Severe adverse reactions represented 1.3% of the subjects treated. Overall, 2.4% (19/779) of subjects discontinued ARAZLO because of local skin reactions.

Table 1:Adverse Reactions Reported by ≥1% of the ARAZLO Group and More Frequently than the Vehicle Group

Adverse Reactions
N (%)
 | ARAZLO N=779 | Vehicle N=791
Application site pain [Application site pain defined as application site stinging, burning or pain] | 41 (5) | 2 (<1)
Application site dryness | 30 (4) | 1 (<1)
Application site exfoliation | 16 (2) | 0 (0)
Application site erythema | 15 (2) | 0 (0)
Application site pruritus | 10 (1) | 0 (0)

Skin irritation was evaluated by active assessment of erythema, scaling, itching, burning and stinging, with grades for none, mild, moderate, or severe. The maximum severity generally peaked at Week 2 of therapy and decreased thereafter. The percentage of subjects with these signs and symptoms at any post-baseline visit are summarized in Table 2.

Table 2: Incidence of Local Cutaneous Irritation at any Post-Baseline Visit

 | ARAZLO Lotion; N=774; Mild/Moderate/Severe | Vehicle Lotion; N=789; Mild/Moderate/Severe
Erythema | 49% | 38%
Scaling | 51% | 23%
Itching | 29% | 14%
Burning | 30% | 6%
Stinging | 22% | 5%

7 DRUG INTERACTIONS

No formal drug-drug interaction studies were conducted with ARAZLO.

Concomitant use with oxidizing agents, as benzoyl peroxide, may cause degradation of tazarotene and may reduce the clinical efficacy of tazarotene.

In a trial of 27 healthy female subjects, between the ages of 20–55 years, receiving a combination oral contraceptive tablet containing 1 mg norethindrone and 35 mcg ethinyl estradiol, the concomitant use of tazarotene administered as 1.1 mg orally (mean ± SD Cmaxand AUC0-24of tazarotenic acid were 28.9 ± 9.4 ng/mL and 120.6 ± 28.5 ng•hr/mL, respectively) did not affect the pharmacokinetics of norethindrone and ethinyl estradiol over a complete cycle.

The impact of tazarotene on the pharmacokinetics of progestin only oral contraceptives (i.e., minipills) has not been evaluated.

8 USE IN SPECIFIC POPULATIONS

8.1 Pregnancy

Risk Summary

ARAZLO is contraindicated in pregnancy.

There are no available data on ARAZLO use in pregnant patients to inform a drug-associated risk of major birth defects, miscarriage or adverse maternal or fetal outcomes. Based on data from animal reproduction studies, retinoid pharmacology, and the potential for systemic absorption, ARAZLO may cause fetal harm when administered to a pregnant patient and is contraindicated during pregnancy. The potential risk to the fetus outweighs the potential benefit to the mother; therefore, ARAZLO should be discontinued as soon as pregnancy is recognized.

In animal reproduction studies with pregnant rats, reduced fetal body weights and reduced skeletal ossification were observed after topical administration of a tazarotene gel formulation during the period of organogenesis at a dose equivalent to the maximum recommended human dose (MRHD) (based on AUC comparison). In animal reproduction studies with pregnant rabbits, single incidences of known retinoid malformations, including spina bifida, hydrocephaly, and heart anomalies were observed after topical administration of a tazarotene gel formulation at 15 times the MRHD (based on AUC comparison) (see Data).

In animal reproduction studies with pregnant rats and rabbits, malformations, fetal toxicity, developmental delays, and/or behavioral delays were observed after oral administration of tazarotene during the period of organogenesis at doses 1 and 30 times, respectively, the MRHD (based on AUC comparison). In pregnant rats, decreased litter size, decreased numbers of live fetuses, decreased fetal body weights, and increased malformations were observed after oral administration of tazarotene prior to mating through early gestation at doses 6 times the MRHD (based on AUC comparison) (see Data).

The estimated background risk of major birth defects and miscarriage for the indicated population is unknown. All pregnancies have a background risk of major birth defects, loss, and other adverse outcomes. In the U.S. general population, the estimated background risk of major birth defects and miscarriage in clinically recognized pregnancies is 2-4% and 15-20%, respectively.

Data

Animal Data

In an embryofetal development study in rats, a tazarotene gel formulation, 0.5% (0.25 mg/kg/day tazarotene) was topically administered to pregnant rats during gestation days 6 through 17. Reduced fetal body weights and reduced skeletal ossification occurred at this dose (equivalent to the MRHD based on AUC comparison). In an embryofetal development study in rabbits, a tazarotene gel formulation, 0.5% (0.25 mg/kg/day tazarotene) was topically administered to pregnant rabbits during gestation days 6 through 18. Single incidences of known retinoid malformations, including spina bifida, hydrocephaly, and heart anomalies were noted at this dose (15 times the MRHD based on AUC comparison).

When tazarotene was given orally to animals, developmental delays were seen in rats; malformations and post- implantation loss were observed in rats and rabbits at doses producing 1 and 30 times, respectively, the MRHD (based on AUC comparison).

In female rats orally administered 2 mg/kg/day of tazarotene from 15 days before mating through gestation day 7, classic developmental effects of retinoids including decreased number of implantation sites, decreased litter size, decreased numbers of live fetuses, and decreased fetal body weights were observed at this dose (6 times the MRHD based on AUC comparison). A low incidence of retinoid-related malformations was observed at this dose.

In a pre- and postnatal development toxicity study, topical administration of a tazarotene gel formulation (0.125 mg/kg/day) to pregnant female rats from gestation day 16 through lactation day 20 reduced pup survival, but did not affect the reproductive capacity of the offspring. Based on data from another study, the systemic drug exposure in the rat at this dose would be equivalent to the MRHD (based on AUC comparison).

8.2 Lactation

Risk Summary

There are no data on the presence of tazarotene or its metabolites in human milk, the effects on the breastfed infant, or the effects on milk production. After single topical doses of a^14C-tazarotene gel formulation to the skin of lactating rats, radioactivity was detected in rat milk. The developmental and health benefits of breastfeeding should be considered along with the mother’s clinical need for ARAZLO and any potential adverse effects on the breastfed child from ARAZLO.

Clinical Considerations

To minimize potential exposure to the breastfed infant via breast milk, use ARAZLO for the shortest duration possible while breastfeeding. Advise breastfeeding patients not to apply ARAZLO directly to the nipple and areola to prevent direct infant exposure.

8.3 Females and Males of Reproductive Potential

Pregnancy Testing

Pregnancy testing is recommended for patients of childbearing potential within 2 weeks prior to initiating ARAZLO therapy which should begin during a menstrual period.

Contraception

Advise patients of childbearing potential to use effective contraception during treatment with ARAZLO.

8.4 Pediatric Use

Safety and effectiveness of ARAZLO for the topical treatment of acne vulgaris have been established in pediatric patients age 9 years and older based on evidence from two multicenter, randomized, double-blind, parallel-group, vehicle-controlled, 12-week clinical trials and an open-label pharmacokinetic study. A total of 300 pediatric subjects aged 9 to less than 17 years received ARAZLO in the clinical studies [see Clinical Pharmacology (12.3)and Clinical Studies (14)] .

The safety and effectiveness of ARAZLO in pediatric patients below the age of 9 years have not been established.

8.5 Geriatric Use

Clinical trials of ARAZLO did not include sufficient numbers of subjects age 65 years and older to determine whether they respond differently from younger subjects.

10 OVERDOSAGE

Oral ingestion of the drug may lead to the same adverse effects as those associated with excessive oral intake of Vitamin A (hypervitaminosis A) or other retinoids. If oral ingestion occurs, monitor the patient closely and administer appropriate supportive measures, as necessary.

11 DESCRIPTION

ARAZLO (tazarotene) is a white to off-white lotion containing 0.045% tazarotene by weight for topical administration.

Tazarotene is a member of the acetylenic class of retinoids. The chemical name for tazarotene is 6-[(3,4-Dihydro-4,4-dimethyl-2H-1-benzothiopyran-6-yl)ethynyl]-3-pyridinecarboxylic acid ethyl ester. The structural formula for tazarotene is represented below:

Tazarotene:

Molecular Formula: C21H21NO2S Molecular Weight: 351.46

Each gram of ARAZLO contains 0.45 mg (0.045%) tazarotene in a white to off-white lotion base consisting of carbomer copolymer type B, carbomer homopolymer type A, diethyl sebacate, edetate disodium dihydrate, light mineral oil, methylparaben, propylparaben, purified water, sodium hydroxide, sorbitan monooleate and sorbitol solution, 70%.

12 CLINICAL PHARMACOLOGY

12.1 Mechanism of Action

Tazarotene is a retinoid prodrug which is converted to its active form, tazarotenic acid, the carboxylic acid of tazarotene, by deesterification. Tazarotenic acid binds to all three members of the retinoic acid receptor (RAR) family: RARα, RARβ and RARγ, but shows relative selectivity for RARβ, and RARγ and may modify gene expression. The clinical significance of these findings for the treatment of acne vulgaris is unknown.

12.3 Pharmacokinetics

Following topical application, tazarotene undergoes esterase hydrolysis to form its active metabolite, tazarotenic acid. Tazarotenic acid is highly bound to plasma proteins (greater than 99%).

Systemic exposure following topical application of ARAZLO was evaluated in 28 subjects in an open-label, randomized, pharmacokinetic study. Subjects aged 9 years and older with moderate to severe acne applied approximately 4 grams of ARAZLO to the entire face (excluding eyes and lips), neck, upper chest, upper back and shoulders once daily for 14 Days.

The majority of collected samples had concentrations below the limit of quantification (LOQ) for tazarotene (0.005 ng/mL). The mean Cmaxand mean AUC(0-t)values for tazarotene from quantifiable samples were 0.007 ng/mL and 0.164 ng•hr/mL on Day 14 to 15, respectively. The mean Cmaxand AUC(0-t)of tazarotene in subjects aged 9 to less than 12 years was approximately 3.7 and 3.6 fold higher, respectively, compared to that observed in subjects 12 years and older.

Tazarotenic acid concentrations were measurable in the majority of samples following single and repeated topical administration of ARAZLO (LOQ = 0.005 ng/mL). The mean Cmaxand AUC(0-t)values for tazarotenic acid from quantifiable samples were 0.365 ng/mL and 5.72 ng•hr/mL on Days 14 to 15, respectively. The mean Cmaxand AUC(0-t)of tazarotenic acid in subjects aged 9 to less than 12 years was approximately 2.4 and 2.3 fold higher, respectively, compared to that observed in subjects 12 years and older.

13 NONCLINICAL TOXICOLOGY

13.1 Carcinogenesis, Mutagenesis, Impairment of Fertility

A long-term study of tazarotene following oral administration of 0.025, 0.050, and 0.125 mg/kg/day to rats showed no indications of increased carcinogenic risks. Based on pharmacokinetic data from a shorter-term study in rats, the highest dose of 0.125 mg/kg/day was anticipated to give systemic exposure in the rat equivalent to the MRHD (based on AUC comparison).

A long-term study with topical application of up to 0.1% of tazarotene in a gel formulation in mice terminated at 88 weeks showed that dose levels of 0.05, 0.125, 0.25, and 1 mg/kg/day (reduced to 0.5 mg/kg/day for males after 41 weeks due to severe dermal irritation) revealed no apparent carcinogenic effects when compared to vehicle control animals. Tazarotenic acid systemic exposures at the highest dose was 7 times the MRHD (based on AUC comparison).

Tazarotene was non-mutagenic in the Ames assay and did not produce structural chromosomal aberrations in human lymphocytes. Tazarotene was non-mutagenic in CHO/HGPRT mammalian cell forward gene mutation assay and was non-clastogenic in an in vivo mouse micronucleus test.

No impairment of fertility occurred in rats when male animals were treated for 70 days prior to mating and female animals were treated for 14 days prior to mating and continuing through gestation and lactation with topical doses of a tazarotene gel formulation up to 0.125 mg/kg/day. Based on data from another study, the systemic drug exposure in the rat at the highest dose was equivalent to the MRHD (based on AUC comparison).

No impairment of mating performance or fertility was observed in male rats treated for 70 days prior to mating with oral doses of tazarotene up to 1 mg/kg/day which produced a systemic exposure 4 times the MRHD (based on AUC comparison).

No impairment of mating performance or fertility was observed in female rats treated for 15 days prior to mating and continuing through gestation day 7 with oral doses of tazarotene up to 2 mg/kg/day. However, there was a significant decrease in the number of estrous stages and an increase in developmental effects at that dose which produced a systemic exposure 6 times the MRHD (based on AUC comparison).

14 CLINICAL STUDIES

The safety and efficacy of once daily use of ARAZLO for the treatment of acne vulgaris were assessed in two multicenter, randomized, double-blind clinical trials in subjects 9 years and older with facial acne vulgaris. Enrolled subjects had a score of moderate (3) or severe (4) on the Evaluator’s Global Severity Score (EGSS), 20 to 50 inflammatory lesions (papules, pustules, and nodules), 25 to 100 non-inflammatory lesions (open and closed comedones) and two or fewer facial nodules. The majority of subjects were White (74%) and female (66%). Approximately 22% were Hispanic/Latino and 42% were younger than 18 years of age. The efficacy endpoints of success on the EGSS, absolute change in noninflammatory lesion count, and absolute change in inflammatory lesion count were assessed at Week 12. Success on the EGSS was defined as at least a 2-grade improvement from Baseline and an EGSS score of clear (0) or almost clear (1). Table 3 lists the efficacy results for trials 1 (NCT03168321) and 2 (NCT03168334).

Table 3: Efficacy Results at Week 12
Trial 1 | ARAZLO Lotion N=402 | Vehicle N=411 | Treatment Difference; (95% Confidence Interval)
EGSS
Clear or Almost Clear and | 25.5% | 13% | 12.5% (7.1%, 17.9%)
2-Grade Reduction from Baseline
Non-Inflammatory Facial Lesions
Mean Absolute Reduction | 21.0 | 16.4 | 4.5 (2.6, 6.4)
Mean Percent Reduction | 51.4% | 41.5%
Inflammatory Facial Lesions
Mean Absolute Reduction | 15.6 | 12.4 | 3.3 (1.9, 4.7)
Mean Percent Reduction | 55.5% | 45.7%
Trial 2 | ARAZLO Lotion N=397 | Vehicle N=404
EGSS
Clear or Almost Clear and; 2-Grade Reduction from Baseline | 29.6% | 17.3% | 12.3% (6.5%, 18.1%)
Non-Inflammatory Facial Lesions
Mean Absolute Reduction | 24.6 | 16.6 | 8.1 (5.9, 10.2)
Mean Percent Reduction | 60% | 41.6%
Inflammatory Facial Lesions
Mean Absolute Reduction | 16.7 | 13.4 | 3.2 (1.9, 4.5)
Mean Percent Reduction | 59.5% | 49%

16 HOW SUPPLIED/STORAGE AND HANDLING

ARAZLO (tazarotene) Lotion, 0.045% is a white to off-white lotion supplied in a white aluminum tube as follows:

- 45 g (NDC 0187-2098-45)

Storage and Handling Conditions

Store at 20° to 25°C (68° to 77°F); excursions permitted to 15° to 30°C (59° to 86°F) [see USP Controlled Room Temperature]. Protect from freezing.

17 PATIENT COUNSELING INFORMATION

Advise the patient to read the FDA-approved patient labeling (Patient Information).

Embryofetal Toxicity

Inform patients of childbearing potential of the potential risk to a fetus. To avoid pregnancy, advise these patients to use effective contraception during treatment with ARAZLO. Advise patients to discontinue the medication if pregnant and to inform their healthcare provider of a known or suspected pregnancy [see Contraindications (4.1), Warnings and Precautions (5.1), and Use in Specific Populations (8.1), (8.3)] .

Lactation

Advise patients to use ARAZLO for the shortest duration possible while breastfeeding. Advise breastfeeding patients not to apply ARAZLO directly to the nipple and areola to avoid direct infant exposure [see Use in Specific Populations (8.2)] .

Skin Irritation

Advise patients to avoid applying ARAZLO to eczematous or sunburned skin. If undue irritation occurs, reduce frequency of application, temporarily interrupt treatment, or discontinue use. Treatment may be resumed once irritation subsides [see Warnings and Precautions (5.2)] .

Photosensitivity and Risk of Sunburn

Advise patients to minimize exposure to sunlight and sunlamps; recommend the use of sunscreen products and protective apparel (e.g., wide-brimmed hat) when sun exposure cannot be avoided. Advise patients to avoid using ARAZLO if also taking other medicines that may increase sensitivity to sunlight [see Warnings and Precautions (5.3)] .

Distributed by:
Bausch Health US, LLC
Bridgewater, NJ 08807 USA

Manufactured by:
Bausch Health Companies Inc.
Laval, Quebec H7L 4A8, Canada

Patented. See https://patents.ortho-dermatologics.com for US patent information.
ARAZLO is a trademark of Bausch Health Companies Inc. or its affiliates.
© 2023 Bausch Health Companies Inc. or its affiliates
9701202

Patient Information

ARAZLO®(ah-RAZ-low)
(tazarotene)
lotion, for topical use

Important information:ARAZLO is for use on skin only. Do not use ARAZLO in your eyes, mouth, the corners of your nose, or vagina.

What is the most important information I should know about ARAZLO?

ARAZLO may cause birth defects if used during pregnancy.

You must not be pregnant when you start using ARAZLO or become pregnant during treatment with ARAZLO.

- For people who are able to get pregnant:
- Your healthcare provider should order a pregnancy test for you within 2 weeks before you begin treatment with ARAZLO to be sure that you are not pregnant. Your healthcare provider will decide when to do the test.
- Begin treatment with ARAZLO during a normal menstrual period.
- Use an effective form of birth control (contraception) during treatment with ARAZLO. Talk with your healthcare provider about birth control options that may be used to prevent pregnancy during treatment with ARAZLO.
- Stop using ARAZLO and tell your healthcare provider right away if you become pregnant during treatment with ARAZLO.

What is ARAZLO?

ARAZLO is a prescription medicine used on the skin (topical) to treat people 9 years of age and older with acne vulgaris.

It is not known if ARAZLO is safe and effective in children under 9 years of age.

Do not use ARAZLO if youare pregnant or plan to become pregnant. See, “What is the most important information I should know about ARAZLO?” at the beginning of this leaflet.

Before using ARAZLO, tell your healthcare provider about all your medical conditions, including if you:

- have eczema or any other skin problems
- are breastfeeding or plan to breastfeed. It is not known if ARAZLO passes into your breast milk. If you use ARAZLO while breastfeeding, use ARAZLO for the shortest time needed. Do not apply ARAZLO directly to the nipple and the areola to avoid your child being exposed to the medicine.

Tell your healthcare provider about all the medicines you take,including prescription and over-the-counter medicines, vitamins, and herbal supplements.

Certain medicines, vitamins, or supplements may make your skin more sensitive to sunlight.Ask your healthcare provider for a list of medicines if you are not sure.

Especially tell your healthcare providerabout any medicines (such as benzoyl peroxide) used on your skin or cosmetics you use, including moisturizers, creams, lotions, or products that can dry out your skin.

Know the medicines you take. Keep a list of them to show to your healthcare provider and pharmacist when you get a new medicine.

How should I use ARAZLO?

- Use ARAZLO exactly as your healthcare provider tells you to use it.
- Apply a thin layer of ARAZLO to cover the affected areas 1 time each day.
- If you use other medicines on your skin such as benzoyl peroxide during treatment with ARAZLO, you should apply one in the morning and one in the evening to separate the application time.
- Do not get ARAZLO in your eyes, the corners of your nose, or in your mouth. If ARAZLO gets in your eyes, rinse them well with water. Call your healthcare provider or get medical help if you have eye irritation that does not go away.
- Wash your hands after applying ARAZLO.

What should I avoid during treatment with ARAZLO?

- Avoid sunlight, including sunlamps during treatment with ARAZLO. ARAZLO can make you more sensitive to the sun, and the light from sunlamps and tanning beds. You could get severe sunburn. Use sunscreen and wear a wide-brimmed hat and clothes that cover your skin if you have to be in sunlight.
- Avoid using cosmetics or topical medicines that may make your skin more sensitive to sunlight or make your skin dry.
- Avoid using ARAZLO on skin with eczema or sunburned skin because it may cause severe irritation.

What are the possible side effects of ARAZLO?

ARAZLO may cause serious side effects, including:

- See, “What is the most important information I should know about ARAZLO?”
- Skin irritation.ARAZLO may cause application site skin pain, dryness, flaking or peeling, redness, and itching. Tell your healthcare provider if you develop any skin irritation during treatment with ARAZLO. If you develop any of these symptoms, your healthcare provider may tell you to use a moisturizer, decrease the number of times you apply ARAZLO, or completely stop treatment with ARAZLO. Also, wind or cold weather may be more irritating to your skin during treatment with ARAZLO.
- Sensitivity to sunlight and risk of sunburn.See, “What should I avoid during treatment with ARAZLO?”
- The most common side effects of ARAZLO includeskin pain, dryness, peeling, redness, and itching.

These are not all the possible side effects of ARAZLO.

Call your doctor for medical advice about side effects. You may report side effects to FDA at 1-800-FDA-1088.

How should I store ARAZLO?

- Store ARAZLO at room temperature between 68°F to 77°F (20°C to 25°C).
- Do not freeze.

Keep ARAZLO and all medicines out of the reach of children.

General information about the safe and effective use of ARAZLO.

Medicines are sometimes prescribed for purposes other than those listed in a Patient Information leaflet. Do not use ARAZLO for a condition for which it was not prescribed. Do not give ARAZLO to other people, even if they have the same symptoms that you have. It may harm them. You can ask your pharmacist or healthcare provider for information about ARAZLO that is written for health professionals.

What are the ingredients in ARAZLO?

Active ingredient:tazarotene

Inactive ingredients:carbomer copolymer type B, carbomer homopolymer type A, diethyl sebacate, edetate disodium dihydrate, light mineral oil, methylparaben, propylparaben, purified water, sodium hydroxide, sorbitan monooleate and sorbitol solution, 70%

Distributed by:Bausch Health US, LLC, Bridgewater, NJ 08807 USA

Manufactured by:Bausch Health Companies Inc., Laval, Quebec H7L 4A8, Canada
Patented. See https://patents.ortho-dermatologics.com for US patent information.

ARAZLO is a trademark of Bausch Health Companies Inc. or its affiliates.

© 2023 Bausch Health Companies Inc. or its affiliates

For more information, call 1-800-321-4576.

- This Patient Information has been approved by the U.S. Food and Drug Administration.
  Revised: 08/2023
  9701202

PACKAGE/LABEL PRINCIPAL DISPLAY PANEL – 45 gram Carton

NDC0187-2098-45

For Topical Use Only
Not For Eye Use
Rx only

ARAZLO®
(tazarotene) Lotion, 0.045%

Net Wt. 45 g

OrthoDermatologics